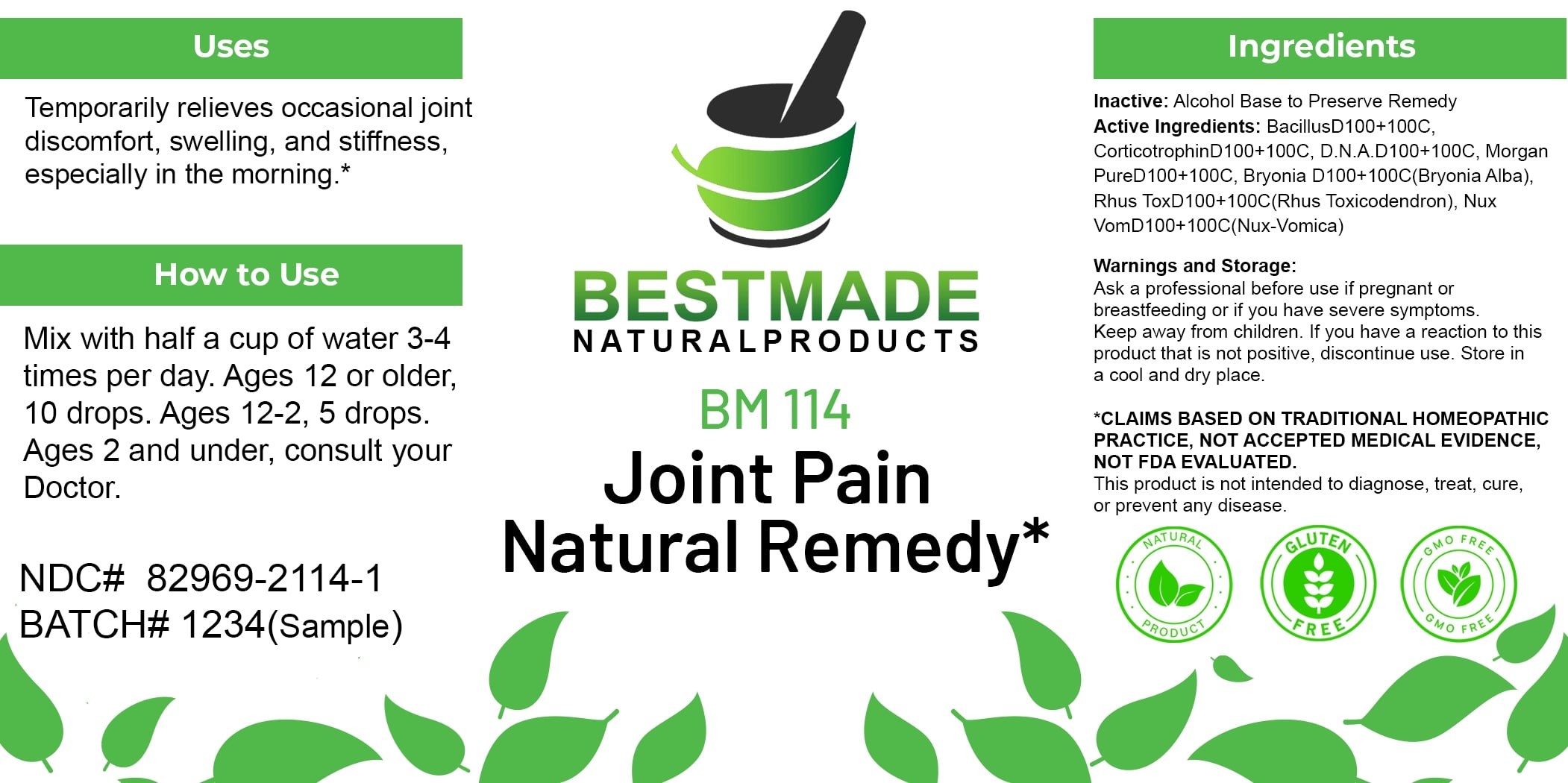 DRUG LABEL: Bestmade Natural Products BM114
NDC: 82969-2114 | Form: LIQUID
Manufacturer: Bestmade Natural Products
Category: homeopathic | Type: HUMAN OTC DRUG LABEL
Date: 20250207

ACTIVE INGREDIENTS: STRYCHNOS NUX-VOMICA SEED 100 [hp_C]/100 [hp_C]; TOXICODENDRON PUBESCENS LEAF 100 [hp_C]/100 [hp_C]; CORTICOTROPIN 100 [hp_C]/100 [hp_C]; ENTEROBACTER CLOACAE 100 [hp_C]/100 [hp_C]; HERRING SPERM DNA 100 [hp_C]/100 [hp_C]; PROTEUS MORGANII 100 [hp_C]/100 [hp_C]; BRYONIA ALBA ROOT 100 [hp_C]/100 [hp_C]
INACTIVE INGREDIENTS: ALCOHOL 100 [hp_C]/100 [hp_C]

BM114

DOSAGE AND ADMINISTRATION

How to Use

Mix with half a cup of water 3-4 times per day. Ages 12 or older, 10 drops. Ages 12-2, 5 drops. Ages 2 and under, consult your Doctor.

INACTIVE INGREDIENT

Ingredients

Inactive: Alcohol Base to Preserve Remedy

ACTIVE INGREDIENT

Active Ingredients: BacillusD100+100C, CorticotrophinD100+100C, D.N.A.D100+100C, Morgan PureD100+100C, Bryonia D100+100C(Bryonia Alba), Rhus ToxD100+100C(Rhus Toxicodendron), Nux VomD100+100C(Nux-Vomica)

Uses

Temporarily relieves occasional joint discomfort, swelling, and stiffness, especially in the morning.*

*CLAIMS BASED ON TRADITIONAL HOMEOPATHIC PRACTICE, NOT ACCEPTED MEDICAL EVIDENCE. NOT FDA EVALUATED.

This product is not intended to diagnose, treat, cure, or prevent any disease.

Uses

Temporarily relieves occasional joint discomfort, swelling, and stiffness, especially in the morning.*

*CLAIMS BASED ON TRADITIONAL HOMEOPATHIC PRACTICE, NOT ACCEPTED MEDICAL EVIDENCE. NOT FDA EVALUATED.

This product is not intended to diagnose, treat, cure, or prevent any disease.

KEEP OUT OF REACH OF CHILDREN

Warnings and Storage:

Ask a professional before use if pregnant or breastfeeding or if you have severe symptoms. Keep away from children. If you have a reaction to this product that is not positive, discontinue use. Store in a cool and dry place.

Warnings and Storage:

Ask a professional before use if pregnant or breastfeeding or if you have severe symptoms. Keep away from children. If you have a reaction to this product that is not positive, discontinue use. Store in a cool and dry place.

*CLAIMS BASED ON TRADITIONAL HOMEOPATHIC PRACTICE, NOT ACCEPTED MEDICAL EVIDENCE. NOT FDA EVALUATED.

This product is not intended to diagnose, treat, cure, or prevent any disease.

Entire package label